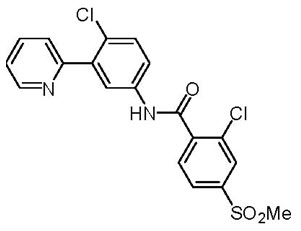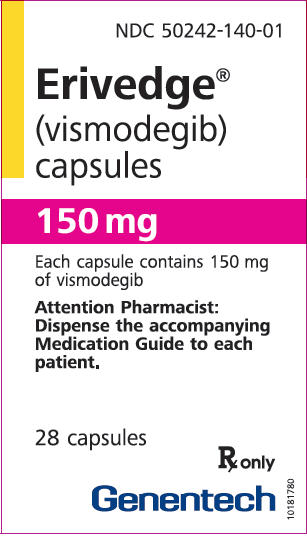 DRUG LABEL: ERIVEDGE
NDC: 50242-140 | Form: CAPSULE
Manufacturer: Genentech, Inc.
Category: prescription | Type: HUMAN PRESCRIPTION DRUG LABEL
Date: 20241202

ACTIVE INGREDIENTS: VISMODEGIB 150 mg/1 1
INACTIVE INGREDIENTS: MICROCRYSTALLINE CELLULOSE; LACTOSE MONOHYDRATE; SODIUM LAURYL SULFATE; POVIDONE K30; SODIUM STARCH GLYCOLATE TYPE A POTATO; TALC; MAGNESIUM STEARATE; GELATIN, UNSPECIFIED; TITANIUM DIOXIDE; FERRIC OXIDE RED; FERROSOFERRIC OXIDE

HIGHLIGHTS OF PRESCRIBING INFORMATION

These highlights do not include all the information needed to use ERIVEDGE safely and effectively. See full prescribing information for ERIVEDGE.
ERIVEDGE® (vismodegib) capsules, for oral use
Initial U.S. Approval: 2012

WARNING: EMBRYO-FETAL TOXICITY

See full prescribing information for complete boxed warning.

- ERIVEDGE can cause embryo-fetal death or severe birth defects when administered to a pregnant woman. ERIVEDGE is embryotoxic, fetotoxic, and teratogenic in animals. Teratogenic effects included severe midline defects, missing digits, and other irreversible malformations. (5.1, 8.1)
- Verify the pregnancy status of females of reproductive potential within 7 days prior to initiating ERIVEDGE. Advise pregnant women of the potential risks to a fetus. Advise females of reproductive potential to use effective contraception during and after ERIVEDGE. (2.1, 5.1, 8.1, 8.3)
- Advise males of the potential risk of ERIVEDGE exposure through semen and to use condoms with a pregnant partner or a female partner of reproductive potential. (5.1, 8.3)

RECENT MAJOR CHANGES

Dosage and Administration (2.3) | 3/2023
Warnings and Precautions (5.3) | 3/2023

1 INDICATIONS AND USAGE

ERIVEDGE® (vismodegib) is a hedgehog pathway inhibitor indicated for the treatment of adults with metastatic basal cell carcinoma, or with locally advanced basal cell carcinoma that has recurred following surgery or who are not candidates for surgery and who are not candidates for radiation. (1)

2 DOSAGE AND ADMINISTRATION

The recommended dosage is 150 mg orally once daily. (2)

3 DOSAGE FORMS AND STRENGTHS

150 mg capsules. (3)

4 CONTRAINDICATIONS

None.

5 WARNINGS AND PRECAUTIONS

- Embryo-Fetal Toxicity:
  - Advise patients not to donate blood or blood products while receiving ERIVEDGE and for 24 months after the final dose of ERIVEDGE (5.1)
  - Advise males not to donate semen during and for 3 months after therapy (5.1, 8.3)
- Severe Cutaneous Adverse Reactions: Permanently discontinue ERIVEDGE in patients with these reactions (5.2)
- Musculoskeletal Adverse Reactions: Temporary dose interruption or discontinuation may be required for these reactions (5.3)
- Premature fusion of the epiphyses (5.4, 8.4)

6 ADVERSE REACTIONS

- The most common adverse reactions (incidence of ≥ 10%) are muscle spasms, alopecia, dysgeusia, weight loss, fatigue, nausea, diarrhea, decreased appetite, constipation, arthralgias, vomiting, and ageusia.

To report SUSPECTED ADVERSE REACTIONS, contact Genentech, Inc. at 1-888-835-2555 or FDA at 1-800-FDA-1088 or www.fda.gov/medwatch.

8 USE IN SPECIFIC POPULATIONS

- Lactation: Breastfeeding not recommended. (8.2)
- Females and Males of Reproductive Potential: May cause amenorrhea in females. (8.3)

FULL PRESCRIBING INFORMATION

WARNING: EMBRYO-FETAL TOXICITY

- ERIVEDGE can cause embryo-fetal death or severe birth defects when administered to a pregnant woman. ERIVEDGE is embryotoxic, fetotoxic, and teratogenic in animals. Teratogenic effects included severe midline defects, missing digits, and other irreversible malformations [see Warnings and Precautions (5.1), Use in Specific Populations (8.1)].
- Verify the pregnancy status of females of reproductive potential within 7 days prior to initiating ERIVEDGE. Advise pregnant women of the potential risks to a fetus. Advise females of reproductive potential to use effective contraception during and after ERIVEDGE [see Dosage and Administration (2.1), Warnings and Precautions (5.1), Use in Specific Populations (8.1, 8.3)].
- Advise males of the potential risk of ERIVEDGE exposure through semen and to use condoms with a pregnant partner or a female partner of reproductive potential [see Warnings and Precautions (5.1), Use in Specific Populations (8.3)].

1 INDICATIONS AND USAGE

ERIVEDGE is indicated for the treatment of adults with metastatic basal cell carcinoma, or with locally advanced basal cell carcinoma that has recurred following surgery or who are not candidates for surgery and who are not candidates for radiation.

2 DOSAGE AND ADMINISTRATION

2.1 Important Safety Information

Verify pregnancy status of females of reproductive potential within 7 days prior to initiating ERIVEDGE [see Use in Specific Populations (8.1, 8.3)].

2.2 Recommended Dosage

The recommended dosage of ERIVEDGE is 150 mg taken orally once daily, with or without food, until disease progression or until unacceptable toxicity.

Swallow capsules whole. Do not open or crush capsules.

If a dose of ERIVEDGE is missed, resume dosing with the next scheduled dose.

2.3 Dosage Modifications for Adverse Reactions

Withhold ERIVEDGE for up to 8 weeks for intolerable adverse reactions until improvement or resolution. Treatment durations shorter than 8 weeks prior to interruptions have not been studied.

Permanently discontinue ERIVEDGE if patients experience severe cutaneous adverse reactions (SCARs) including Stevens-Johnson syndrome (SJS), toxic epidermal necrolysis (TEN), or drug reaction with eosinophilia and systemic symptoms (DRESS) [see Warnings and Precautions (5.2)].

Interrupt ERIVEDGE for severe or intolerable musculoskeletal adverse reactions. Permanently discontinue ERIVEDGE for recurrent, severe or intolerable musculoskeletal adverse reactions [see Warnings and Precautions (5.3)].

3 DOSAGE FORMS AND STRENGTHS

Capsules: 150 mg with "150 mg" printed on pink opaque body and "VISMO" printed on grey opaque cap in black ink.

4 CONTRAINDICATIONS

None.

5 WARNINGS AND PRECAUTIONS

5.1 Embryo-Fetal Toxicity

Based on its mechanism of action, ERIVEDGE can cause embryo-fetal death or severe birth defects when administered to a pregnant woman. In animal reproduction studies, vismodegib was embryotoxic, fetotoxic, and teratogenic at maternal exposures lower than the human exposures at the recommended dose of 150 mg once daily [see Use in Specific Populations (8.1)].

Females of Reproductive Potential

Verify the pregnancy status of females of reproductive potential within 7 days prior to initiating ERIVEDGE. Advise pregnant women of the potential risk to a fetus. Advise females of reproductive potential to use effective contraception during therapy with ERIVEDGE and for 24 months after the final dose [see Use in Specific Populations (8.1, 8.3)].

Males

Vismodegib is present in semen. It is not known if the amount of vismodegib in semen can cause embryo-fetal harm. Advise males to use condoms, even after a vasectomy, to avoid potential drug exposure in pregnant partners and female partners of reproductive potential during therapy and for 3 months after the final dose of ERIVEDGE. Advise male patients not to donate semen during and for 3 months after the final dose of ERIVEDGE [see Use in Specific Populations (8.3)].

Blood Donation

Advise patients not to donate blood or blood products while receiving ERIVEDGE and for 24 months after the final dose of ERIVEDGE.

5.2 Severe Cutaneous Adverse Reactions

Severe cutaneous adverse reactions (SCARs), including Stevens-Johnson syndrome (SJS), toxic epidermal necrolysis (TEN) and drug reaction with eosinophilia and systemic symptoms (DRESS), which can be life-threatening or fatal, have been reported during treatment with ERIVEDGE [see Adverse Reactions (6.2)].

Permanently discontinue ERIVEDGE in patients with these reactions [see Dosage and Administration (2.3)].

5.3 Musculoskeletal Adverse Reactions

Musculoskeletal adverse reactions, which may be accompanied by serum creatine phosphokinase (CPK) elevations, have occurred with ERIVEDGE and other drugs which inhibit the hedgehog (Hh) pathway. In the pooled safety population in clinical trials of ERIVEDGE, musculoskeletal and connective tissue adverse reactions occurred in 78% of patients treated, with 7% (9/138) reported as Grade 3. The most frequent manifestations of musculoskeletal and connective tissue adverse reactions (all grades) reported were muscle spasms (72%) and arthralgias (16%). In a post-approval clinical trial of 1232 patients, Grade 3 or 4 elevations in serum CPK laboratory values occurred in 2.4% of the 453 patients who had any CPK measurement [see Adverse Reactions (6.1)].

Obtain baseline serum creatine phosphokinase (CPK) and creatinine levels and as clinically indicated (e.g., if muscle symptoms are reported). Depending on the severity of symptoms, temporary dose interruption or discontinuation may be required for musculoskeletal adverse reactions or serum CPK elevation [see Dosage and Administration (2.3)].

5.4 Premature Fusion of the Epiphyses

Premature fusion of the epiphyses has been reported in pediatric patients exposed to ERIVEDGE. In some cases, fusion progressed after drug discontinuation [see Use in Specific Populations (8.4)]. ERIVEDGE is not indicated for pediatric patients.

6 ADVERSE REACTIONS

The following clinically significant adverse reactions are described elsewhere in the labeling:

- Embryo-Fetal Toxicity [see Warnings and Precautions (5.1)]
- Severe Cutaneous Adverse Reactions [see Warnings and Precautions (5.2)]
- Musculoskeletal Adverse Reactions [see Warnings and Precautions (5.3)]
- Premature Fusion of the Epiphyses [see Warnings and Precautions (5.4)]

6.1 Clinical Trials Experience

Because clinical trials are conducted under widely varying conditions, adverse reaction rates observed in the clinical trials of a drug cannot be directly compared to rates in the clinical trials of another drug and may not reflect the rates observed in clinical practice.

The safety data described below reflect exposure to ERIVEDGE in 138 patients with advanced basal cell carcinoma (BCC) who received ERIVEDGE at doses ≥ 150 mg orally daily in four open-label, uncontrolled, dose-ranging or fixed single dose clinical trials [Study SHH3925g, SHH4437g, SHH4476g and SHH4610g]. The median age of these patients was 61 years (range 21 to 101 years), 100% were White (including Hispanics), and 64% were male. The median duration of treatment was approximately 10 months (range 21 days to 36 months); 111 patients received ERIVEDGE for 6 months or longer.

The most common adverse reactions (≥ 10%) were muscle spasms, alopecia, dysgeusia, weight loss, fatigue, nausea, diarrhea, decreased appetite, constipation, arthralgias, vomiting, and ageusia (Table 1).

Table 1: Adverse Reactions Occurring in ≥ 10% of Patients with Advanced Basal Cell Carcinoma
Adverse Reaction | ERIVEDGE (N = 138)
Adverse Reaction | All Grades [Grading according to National Cancer Institute-Common Terminology Criteria for Adverse Events version 3.0.] (%) | Grade 3 (%) | Grade 4 (%)
Gastrointestinal
Nausea | 30% | 0.7% | -
Diarrhea | 29% | 0.7% | -
Constipation | 21% | - | -
Vomiting | 14% | - | -
General
Fatigue | 40% | 5% | 0.7%
Investigations
Weight loss | 45% | 7% | -
Metabolism and nutrition
Decreased appetite | 25% | 2.2% | -
Musculoskeletal and connective tissue
Muscle spasms | 72% | 3.6% | -
Arthralgias | 16% | 0.7%
Nervous system
Dysgeusia | 55% | - | -
Ageusia | 11% | - | -
Skin and subcutaneous tissue
Alopecia | 64% | - | -

Amenorrhea

Among patients from the clinical trials included in the pooled safety data analysis, 30% of 10 pre-menopausal women developed amenorrhea while receiving ERIVEDGE.

Laboratory Abnormalities

Grade 3 laboratory abnormalities observed in clinical trials were hyponatremia (4%), azotemia (2%) and hypokalemia (1%).

Additionally, in a post-approval clinical trial conducted in 1232 patients with locally advanced or metastatic BCC treated with ERIVEDGE, a subset of 29 patients had baseline values for blood creatine phosphokinase (CPK) reported. Within this subset of patients, 38% had a shift from baseline, including Grade 3 (3%) increased CPK. Grade 3 or 4 increased CPK occurred in 2.4% of the 453 patients across the entire study population with any CPK measurement.

6.2 Postmarketing Experience

The following adverse reactions have been identified during post-approval use of ERIVEDGE. Because these reactions are reported voluntarily from a population of uncertain size, it is not always possible to reliably estimate their frequency or establish a causal relationship to drug exposure.

Hepatobiliary disorders: Drug-induced liver injury

Skin and subcutaneous tissue disorders: Stevens-Johnson syndrome/toxic epidermal necrolysis, drug reaction with eosinophilia and systemic symptoms [see Warnings and Precautions (5.2)].

8 USE IN SPECIFIC POPULATIONS

8.1 Pregnancy

Pregnancy Exposure Registry

There is a pregnancy exposure registry that monitors pregnancy outcomes in women exposed to ERIVEDGE during pregnancy. Report pregnancies to Genentech at 1-888-835-2555.

Risk Summary

Based on its mechanism of action and findings from animal reproduction studies, ERIVEDGE can cause fetal harm when administered to a pregnant woman [see Clinical Pharmacology (12.1)]. In animal reproduction studies, oral administration of vismodegib during organogenesis at doses below the 150 mg clinical dose resulted in embryotoxicity, fetotoxicity, and teratogenicity in rats (see Data). There are no human data on the use of ERIVEDGE in pregnant women. Advise pregnant women of the potential risk to a fetus.

In the U.S. general population, the estimated background risk of major birth defects and miscarriage in clinically recognized pregnancies is 2-4% and 15-20%, respectively.

Data

Animal Data

In an embryo-fetal toxicity study, pregnant rats were administered vismodegib orally at doses of 10, 60, or 300 mg/kg/day during the period of organogenesis. Pre- and post-implantation loss were increased at doses of ≥ 60 mg/kg/day [approximately 2 times the human exposure at the 150 mg clinical dose based on area under the curve (AUC)], which included early resorption of 100% of the fetuses. A dose of 10 mg/kg/day [approximately 0.2 times the human exposure (AUC) at the recommended 150 mg clinical dose] resulted in malformations (including missing and/or fused digits, open perineum and craniofacial anomalies) and retardations or variations (including dilated renal pelvis, dilated ureter, and incompletely or unossified sternal elements, centra of vertebrae, or proximal phalanges and claws).

8.2 Lactation

No data are available regarding the presence of vismodegib in human milk, the effects of the drug on the breastfed child, or the effects of the drug on milk production. Because of the potential for serious adverse reactions in breastfed infants from ERIVEDGE, advise women that breastfeeding is not recommended during therapy with ERIVEDGE and for 24 months after the final dose.

8.3 Females and Males of Reproductive Potential

Pregnancy Testing

Verify the pregnancy status of females of reproductive potential within 7 days prior to initiating ERIVEDGE.

Contraception

Based on its mechanism of action and animal data, ERIVEDGE can cause fetal harm when administered to a pregnant woman [see Use in Specific Populations (8.1)].

Females

Advise females of reproductive potential to use effective contraception during therapy with ERIVEDGE and for 24 months after the final dose.

Males

Vismodegib is present in semen [see Clinical Pharmacology (12.3)]. It is not known if the amount of vismodegib in semen can cause embryo-fetal harm. Advise male patients to use condoms, even after a vasectomy, to avoid drug exposure to pregnant partners and female partners of reproductive potential during therapy with and for 3 months after the final dose of ERIVEDGE. Advise males of the potential risk to an embryo or fetus if a female partner of reproductive potential is exposed to ERIVEDGE. Advise males not to donate semen during therapy with ERIVEDGE and for 3 months after the final dose.

Infertility

Females

Amenorrhea can occur in females of reproductive potential. Reversibility of amenorrhea is unknown [see Adverse Reactions (6.1)].

8.4 Pediatric Use

The safety and effectiveness of ERIVEDGE have not been established in pediatric patients.

Premature fusion of the epiphyses [see Warnings and Precautions (5.3)] and precocious puberty have been reported in pediatric patients exposed to ERIVEDGE. In some cases, epiphyseal fusion progressed after drug discontinuation.

Juvenile Animal Toxicity Data

In repeat-dose toxicology studies in rats, administration of oral vismodegib resulted in toxicities in bone and teeth. Effects on bone consisted of closure of the epiphyseal growth plate when oral vismodegib was administered for 26 weeks at ≥ 50 mg/kg/day (approximately ≥ 0.4 times the human exposure (AUC) at the 150 mg clinical dose). Abnormalities in growing incisor teeth (including degeneration/necrosis of odontoblasts, formation of fluid-filled cysts in the dental pulp, ossification of the root canal, and hemorrhage resulting in breakage or loss of teeth) were observed after administration of oral vismodegib at ≥ 15 mg/kg/day (approximately ≥ 0.2 times the human exposure (AUC) at the 150 mg clinical dose).

8.5 Geriatric Use

Clinical studies of ERIVEDGE did not include sufficient numbers of patients aged 65 and over to determine whether they respond differently from younger patients.

8.6 Hepatic Impairment

No dose adjustment is required in patients with hepatic impairment [see Clinical Pharmacology (12.3)].

8.7 Renal Impairment

No dose adjustment is required in patients with renal impairment [see Clinical Pharmacology (12.3)].

11 DESCRIPTION

Vismodegib is a hedgehog (Hh) pathway inhibitor, which is described chemically as 2-Chloro-N-(4-chloro-3-(pyridin-2-yl)phenyl)-4-(methylsulfonyl)benzamide. The molecular formula is C19H14Cl2N2O3S. The molecular weight is 421.3 g/mol and the structural formula is:

Vismodegib is a crystalline free base with a pKa (pyridinium cation) of 3.8, appearing as a white to tan powder. The solubility of vismodegib is pH dependent with 0.1 µg/mL at pH 7 and 0.99 mg/mL at pH 1. The partition coefficient (log P) is 2.7.

ERIVEDGE (vismodegib) for oral administration is supplied in capsules containing 150 mg vismodegib and the following inactive ingredients: microcrystalline cellulose, lactose monohydrate, sodium lauryl sulfate, povidone, sodium starch glycolate, talc, and magnesium stearate (non-bovine). The capsule shell contains gelatin, titanium dioxide, red iron oxide, and black iron oxide. The black printing ink contains shellac and black iron oxide.

12 CLINICAL PHARMACOLOGY

12.1 Mechanism of Action

Vismodegib is an inhibitor of the Hedgehog pathway. Vismodegib binds to and inhibits Smoothened, a transmembrane protein involved in Hedgehog signal transduction.

12.2 Pharmacodynamics

Cardiac Electrophysiology

ERIVEDGE did not prolong the QT interval to any clinically relevant extent following 7 days of 150 mg once-daily dosing (at steady state) .

12.3 Pharmacokinetics

The pharmacokinetics of vismodegib were studied in healthy subjects and patients. Following daily oral dosing, the pharmacokinetics of vismodegib appear to be nonlinear with steady state achieved within 7 days. Increasing the dose from 150 mg to 540 mg (1 to 3.6 times the recommended dose) does not result in higher steady state plasma concentrations. Average plasma concentration of vismodegib at steady state (Css,avg) is ~23 µM following 150 mg once daily dose.

Absorption

The single dose absolute bioavailability of vismodegib is 32%. Absorption is saturable as evidenced by the lack of dose proportional increase in exposure after a single dose of 270 mg or 540 mg vismodegib.

Effect of Food

Cmax and AUC0-24hr of vismodegib at steady state are not affected by food.

Distribution

The volume of distribution of vismodegib ranges from 16.4 to 26.6 L. Vismodegib plasma protein binding in patients is > 99%. Vismodegib binds to both human serum albumin and alpha-1-acid glycoprotein (AAG) and binding to AAG is saturable.

Male patients had an average concentration of vismodegib in semen on day 8 that was 6.5% of the average steady state concentration (Css) observed in plasma.

Elimination

The estimated elimination half-life (t1/2) of vismodegib is 4 days after continuous once-daily dosing and 12 days after a single dose.

Metabolism

Greater than 98% of the total circulating drug-related components are the parent drug. Metabolic pathways of vismodegib in humans include oxidation, glucuronidation, and pyridine ring cleavage. The two most abundant oxidative metabolites recovered in feces are produced in vitro by recombinant CYP2C9 and CYP3A.

Excretion

Vismodegib and its metabolites are eliminated primarily by the hepatic route with 82% of the administered dose recovered in the feces and 4.4% recovered in urine.

Specific Populations

Weight (41-140 kg), age (26-89 years), sex, mild to moderate renal impairment (creatinine clearance of 30 to 79 mL/min), mild hepatic impairment (normal total bilirubin and aspartate transaminase (AST) > upper limit of normal (ULN) or total bilirubin > 1 to 1.5 times ULN), moderate hepatic impairment (total bilirubin > 1.5 to 3 times ULN), or severe hepatic impairment (total bilirubin > 3 to 10 times ULN) had no clinically relevant effects on the systemic exposure of vismodegib. The impact of severe renal impairment on the pharmacokinetics of vismodegib is unknown.

Drug Interaction Studies

Clinical Studies

No clinically significant differences in vismodegib pharmacokinetics were observed when used concomitantly with fluconazole (moderate CYP2C9 and CYP3A4 inhibitor), itraconazole (strong CYP3A4 inhibitor and P-gp inhibitor) and rabeprazole (gastric acid reducing agent, proton pump inhibitor).

No clinically significant differences in the pharmacokinetics of the following drugs were observed when used concomitantly with vismodegib: rosiglitazone (a CYP2C8 substrate) or ethinyl estradiol and norethindrone (oral contraceptive).

In Vitro Studies

Vismodegib is an inhibitor of the transporter BCRP and is not an inducer of CYP1A2, CYP2B6, or CYP3A.

13 NONCLINICAL TOXICOLOGY

13.1 Carcinogenesis, Mutagenesis, Impairment of Fertility

Carcinogenicity studies were performed in mice and rats. No carcinogenic potential was identified in either species. Vismodegib was not mutagenic in the in vitro bacterial reverse mutation (Ames) assay and was not clastogenic in the in vitro human chromosomal aberration assay in human peripheral blood lymphocytes or in the in vivo rat bone marrow micronucleus assay.

In a dedicated 26-week rat fertility study, no effects on male reproductive organs or fertility endpoints were observed at vismodegib doses of 100 mg/kg/day [approximately 1.3 times the human exposure (steady state AUC0-24hr) at the 150 mg clinical dose] either at the end of dosing or following a 16-week recovery phase. While there were increased numbers of degenerating germ cells and hypospermia in sexually immature dogs observed at ≥ 50 mg/kg/day in the 4-week general toxicity study, there were no effects on male reproductive organs in sexually mature rats and dogs, in the vismodegib general toxicity studies of up to 26-weeks.

In a female fertility study, treatment of rats with vismodegib at 100 mg/kg/day [approximately 1.2-times the human exposure (steady state AUC0-24hr) at the 150 mg clinical dose] for 26-weeks prior to mating resulted in decreased implantations, increased percent preimplantation loss, and decreased numbers of dams with viable embryos. No vismodegib-related changes in fertility were observed following a 16-week recovery period. In a 26-week general toxicity study in rats, decreased numbers of corpora lutea were observed at 100 mg/kg/day; the effect was not reversed by the end of an 8-week recovery period.

13.2 Animal Toxicology and/or Pharmacology

Neurologic effects characterized as limb or body tremors or twitching were observed in rats administered oral vismodegib for 4 weeks or longer at ≥ 50 mg/kg/day (approximately ≥ 0.4 times the human exposure (AUC) at the 150 mg clinical dose). These observations resolved upon discontinuation of dosing and were not associated with microscopic findings.

14 CLINICAL STUDIES

A single, international, single-arm, multi-center, open-label, 2-cohort trial [SHH4476g (NCT00833417)] was conducted in 104 patients with either metastatic basal cell carcinoma (mBCC) (n = 33) or locally advanced BCC (laBCC) (n = 71). Patients with laBCC were required to have lesions that had recurred after radiotherapy, unless radiotherapy was contraindicated or inappropriate (e.g. Gorlin syndrome; limitations because of location of tumor or cumulative prior radiotherapy dose), and where the lesions were either unresectable or surgical resection would result in substantial deformity. Patients were to receive ERIVEDGE 150 mg orally once daily until disease progression or unacceptable toxicity.

The major efficacy outcome measure was objective response rate (ORR) as assessed by an independent review facility (IRF). In the mBCC cohort, tumor response was assessed according to the Response Evaluation Criteria in Solid Tumors (RECIST) version 1.0. In the laBCC cohort, tumor response evaluation included measurement of externally assessable tumor (including scar) and assessment for ulceration in photographs, radiographic assessment of target lesions (if appropriate), and tumor biopsy. An objective response in laBCC required at least one of the following criteria and absence of any criterion for disease progression: (1) ≥ 30% reduction in lesion size [sum of the longest diameter (SLD)] from baseline in target lesions by radiographic assessment; (2) ≥ 30% reduction in SLD from baseline in externally visible dimension of target lesions; (3) complete resolution of ulceration in all target lesions. Complete response was defined as objective response (as defined above) with no residual BCC on sampling tumor biopsy. Disease progression was defined as any of the following: (1) ≥ 20% increase in the SLD from nadir in target lesions (either by radiography or by externally visible dimension); (2) new ulceration of target lesions persisting without evidence of healing for at least 2 weeks; (3) new lesions by radiographic assessment or physical examination; (4) progression of non-target lesions by RECIST.

Of the 104 patients enrolled, 96 patients were evaluable for ORR. Twenty-one percent of patients carried a diagnosis of Gorlin syndrome. The median age of the efficacy evaluable population was 62 years (46% were at least 65 years old), 61% male and 100% White. For the mBCC cohort (n = 33), 97% of patients had prior therapy including surgery (97%), radiotherapy (58%), and systemic therapies (30%). For the laBCC cohort (n = 63), 94% of patients had prior therapies including surgery (89%), radiotherapy (27%), and systemic/topical therapies (11%). The median duration of treatment was 10.2 months (range 0.7 to 18.7 months).

The efficacy results are presented in Table 2.

Table 2: Efficacy Results for Evaluable Patients in Study SHH4476g [Patients who received at least one dose of ERIVEDGE with independent pathologist-confirmed diagnosis of BCC]
 | mBCC (n = 33) | laBCC (n = 63)
IRF [IRF = Independent Review Facility] -Confirmed ORR, n (%) | 10 (30.3) | 27 (42.9)
(95% CI) | (15.6, 48.2) | (30.5, 56.0)
Complete response [For laBCC, complete response was defined as objective response with no residual BCC on sampling tumor biopsy.] | 0 (0.0) | 13 (20.6)
Partial response | 10 (30.3) | 14 (22.2)
Median Response Duration (months) | 7.6 | 7.6
(95% CI [CI = Confidence Interval]) | (5.6, NE [NE = Not estimable]) | (5.7, 9.7)

16 HOW SUPPLIED/STORAGE AND HANDLING

ERIVEDGE capsules have a pink opaque body and a grey opaque cap with "150 mg" printed on the capsule body and "VISMO" printed on the capsule cap in black ink.

ERIVEDGE capsules are available in bottles of 28 capsules (NDC 50242-140-01).

STORAGE AND HANDLING

Store at room temperature 20°C to 25°C (68°F to 77°F); excursions permitted between 15°C to 30°C (59°F to 86°F) [see USP Controlled Room Temperature].

Keep the bottle tightly closed to protect from moisture.

17 PATIENT COUNSELING INFORMATION

Advise the patient to read the FDA-approved patient labeling (Medication Guide).

Embryo-Fetal Toxicity [see Warnings and Precautions (5.1), Use in Specific Populations (8.1, 8.3)]

Females of Reproductive Potential

- Advise women of the potential risk to a fetus. Advise female patients and female partners of male patients to contact their healthcare provider with a known or suspected pregnancy.
- Inform females there is a Pregnancy Exposure Registry that monitors pregnancy outcomes in females exposed to ERIVEDGE during pregnancy and that they can contact the Pregnancy Exposure Registry by calling 1-888-835-2555.
- Advise females of reproductive potential to use effective contraception during therapy with ERIVEDGE and for 24 months after the final dose.

Males

- Advise males, even those with prior vasectomy, to use condoms to avoid potential drug exposure in both pregnant partners and female partners of reproductive potential during therapy with ERIVEDGE and for 3 months after the final dose.
- Advise males not to donate semen during therapy with ERIVEDGE and for 3 months after the final dose.

Blood Donation

- Advise patients not to donate blood or blood products during therapy with ERIVEDGE and for 24 months after the final dose.

Lactation

- Advise women not to breastfeed during therapy with ERIVEDGE and for 24 months after the final dose [see Use in Specific Populations (8.2)].

Severe Cutaneous Reactions

- Inform patients of the signs and symptoms of severe cutaneous reactions. Advise patients to contact their healthcare provider immediately for signs and symptoms of severe cutaneous reactions [see Warnings and Precautions (5.2)].

Muscle-related adverse reactions

- Advise patients starting therapy with ERIVEDGE of the risk of muscle-related adverse reactions. Advise patients to contact their healthcare provider immediately for any new unexplained muscle pain, tenderness, or weakness occurring during treatment or that persists after discontinuing ERIVEDGE [see Warnings and Precautions (5.3)]

ERIVEDGE® (vismodegib) capsules

Manufactured by:
Patheon, Inc.
Mississauga, Canada

Distributed by:
Genentech USA, Inc.
A Member of the Roche Group
1 DNA Way
South San Francisco, CA 94080-4990

ERIVEDGE is a registered trademark of Genentech, Inc.
©2023 Genentech, Inc. All rights reserved.

MEDICATION GUIDE
ERIVEDGE® (EH-rih-vej)
(vismodegib)
Capsule

What is the most important information I should know about ERIVEDGE?
ERIVEDGE can cause your baby to die before it is born (be stillborn) or cause your baby to have severe birth defects.
For females who can become pregnant:

- You should talk with your healthcare provider about the risks of ERIVEDGE to your unborn child.
- Your healthcare provider will do a pregnancy test within 7 days before you start taking ERIVEDGE.
- In order to avoid pregnancy, you should use birth control during treatment and for 24 months after your final dose of ERIVEDGE. Talk with your healthcare provider about what birth control method is right for you during this time.
- Talk to your healthcare provider right away if you have unprotected sex or if you think that your birth control has failed.
- Tell your healthcare provider right away if you become pregnant or think that you may be pregnant.

For males:

- ERIVEDGE is present in semen. Do not donate semen while you are taking ERIVEDGE and for 3 months after your final dose.
- You should always use a condom, even if you have had a vasectomy, during sex with female partners who are pregnant or who are able to become pregnant, during treatment with ERIVEDGE and for 3 months after your final dose to protect your female partner from being exposed to ERIVEDGE.
- Tell your healthcare provider right away if your partner becomes pregnant or thinks she is pregnant while you are taking ERIVEDGE.

Pregnancy Exposure Registry:
There is a Pregnancy Exposure Registry for females taking ERIVEDGE who become pregnant. The purpose of this registry is to monitor the health of you and your unborn baby. If you think that you or your female partner may have been exposed to ERIVEDGE during pregnancy, talk to your healthcare provider right away. If you become pregnant during treatment with ERIVEDGE, you or your healthcare provider should report your pregnancy to Genentech at 1-888-835-2555.

What is ERIVEDGE?
ERIVEDGE is a prescription medicine used to treat adults with a type of skin cancer, called basal cell carcinoma, that has spread to other parts of the body, or that has come back after surgery or that your healthcare provider decides cannot be treated with surgery or radiation.
It is not known if ERIVEDGE is safe and effective in children.

Before taking ERIVEDGE, tell your healthcare provider about all of your medical conditions, including if you:

- are pregnant or plan to become pregnant. See "What is the most important information I should know about ERIVEDGE?"
- are breastfeeding or plan to breastfeed. It is not known if ERIVEDGE passes into your breast milk. You should not breastfeed during treatment and for 24 months after your final dose of ERIVEDGE. Talk to your healthcare provider about the best way to feed your baby during this time.

Tell your healthcare provider about all the medicines you take, including prescription and over-the-counter medicines, vitamins, and herbal supplements.

How should I take ERIVEDGE?

- Take ERIVEDGE exactly as your healthcare provider tells you.
- You can take ERIVEDGE with or without food.
- Swallow ERIVEDGE capsules whole. Do not open or crush the capsules.
- Take ERIVEDGE 1 time each day.
- If you miss a dose, skip the missed dose. Just take your next scheduled dose.
- Your healthcare provider will perform certain tests to check you for side effects before and during treatment with ERIVEDGE.
- Your healthcare provider may temporarily or permanently stop treatment with ERIVEDGE if you have certain side effects. Do not stop taking ERIVEDGE unless your healthcare provider tells you to.

What should I avoid while taking ERIVEDGE?

- Do not donate blood or blood products while you are taking ERIVEDGE and for 24 months after your final dose.
- For Males: Do not donate semen while you are taking ERIVEDGE and for 3 months after your final dose.

What are the possible side effects of ERIVEDGE?
ERIVEDGE can cause serious side effects, including:

- See "What is the most important information I should know about ERIVEDGE?"

- Severe skin reactions. Severe skin reactions have happened in some people taking ERIVEDGE. You may need to be treated in a hospital because these severe skin reactions can be life-threatening or lead to death.
  Tell your healthcare provider right away if you develop any of the following signs or symptoms of a severe skin reaction, including:

- blisters or peeling of your skin
- blisters on your lip, or around your mouth or eyes
- mouth sores or genital sores

- high fever or flu-like symptoms
- enlarged lymph nodes
- skin pain and burning

Your healthcare provider may permanently stop ERIVEDGE if you develop a severe skin reaction.

- Muscle Problems. Muscle problems are common with ERIVEDGE, but can also sometimes be serious. ERIVEDGE can increase your risk of muscle spasms or muscle pain. Tell your healthcare provider right away if you develop any new or worsening muscle pain, tenderness, or weakness during or after treatment with ERIVEDGE. Your healthcare provider should do a blood test to check for muscle problems and to check your kidney function before you start taking ERIVEDGE, and as needed during treatment if you develop muscle problems.

- Bone growth problems. Bone growth problems have happened in children who have been exposed to ERIVEDGE. These problems may continue even after stopping treatment with ERIVEDGE.

The common side effects of ERIVEDGE are:

- muscle spasms
- hair loss
- change in how things taste or loss of taste
- weight loss
- tiredness

- nausea
- diarrhea
- decreased appetite
- constipation
- joint pain
- vomiting

ERIVEDGE can cause absence of menstrual periods (amenorrhea) in females who are able to become pregnant. It is not known if amenorrhea is permanent. Talk to your healthcare provider if you have concerns about fertility.
These are not all the possible side effects of ERIVEDGE.
Call your doctor for medical advice about side effects. You may report side effects to FDA at 1-800-FDA-1088.
You may also report side effects to Genentech, Inc. at 1-888-835-2555.

How should I store ERIVEDGE?

- Store ERIVEDGE at room temperature between 68°F to 77°F (20°C to 25°C).
- Keep the bottle tightly closed to protect ERIVEDGE from moisture.

Keep ERIVEDGE and all medicines out of the reach of children.

General information about the safe and effective use of ERIVEDGE.
Medicines are sometimes prescribed for purposes other than those listed in a Medication Guide. Do not use ERIVEDGE for a condition for which it was not prescribed. Do not give ERIVEDGE to other people, even if they have the same symptoms that you have. It may harm them. You can ask your pharmacist or healthcare provider for information about ERIVEDGE that is written for health professionals.

What are the ingredients in ERIVEDGE?
Active ingredient: vismodegib
Inactive ingredients: microcrystalline cellulose, lactose monohydrate, sodium lauryl sulfate, povidone, sodium starch glycolate, talc, and magnesium stearate (non-bovine). The capsule shell contains gelatin, titanium dioxide, red iron oxide, and black iron oxide. The black printing ink contains shellac and black iron oxide.
Manufactured by: Patheon, Inc. Mississauga, Canada
Distributed by: Genentech USA, Inc. A Member of the Roche Group 1 DNA Way South San Francisco, CA 94080-4990
ERIVEDGE is a registered trademark of Genentech, Inc.
©2023 Genentech, Inc.
For more information, call 1-855-737-4833 or go to www.erivedge.com

This Medication Guide has been approved by the U.S. Food and Drug Administration.

Revised: March 2023

Representative sample of labeling (see the HOW SUPPLIED section for complete listing):

PRINCIPAL DISPLAY PANEL - 150 mg Capsule Bottle Carton

NDC 50242-140-01

Erivedge®
(vismodegib)
capsules

150 mg

Each capsule contains 150 mg
of vismodegib

Attention Pharmacist:
Dispense the accompanying
Medication Guide to each
patient.

28 capsules

Rx only

Genentech

10181780